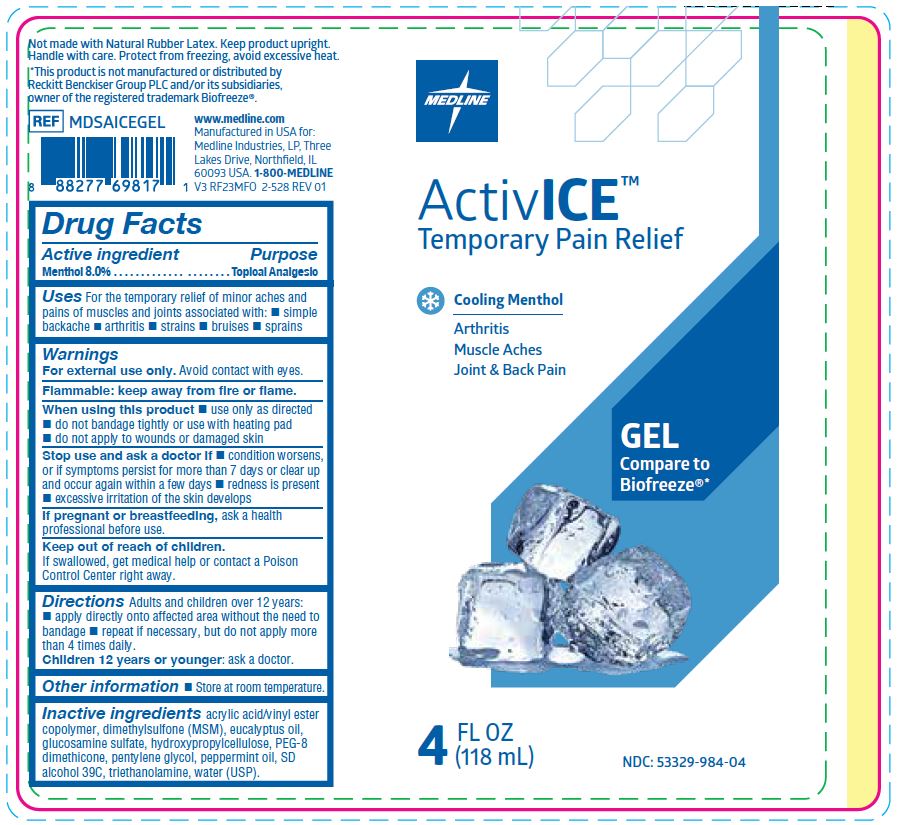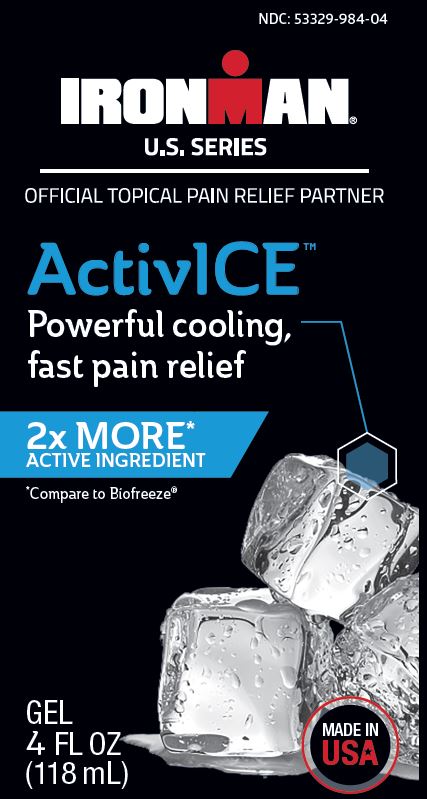 DRUG LABEL: ActivICE
NDC: 53329-984 | Form: GEL
Manufacturer: Medline Industries, LP
Category: otc | Type: HUMAN OTC DRUG LABEL
Date: 20241212

ACTIVE INGREDIENTS: MENTHOL 80 mg/1 mL
INACTIVE INGREDIENTS: PENTYLENE GLYCOL; WATER; PEG-8 DIMETHICONE; TROLAMINE; PEPPERMINT OIL; ALCOHOL; HYDROXYPROPYL CELLULOSE (1600000 WAMW); EUCALYPTUS OIL; GLUCOSAMINE SULFATE; DIMETHYL SULFONE

984 ActivIce gel

Active ingredient

Menthol 8.0%

Purpose

Topical Analgesic

Uses

For the temporary relief of minor aches and pains of muscles and joints associated with:

- simple backache
- arthritis
- strains
- bruises
- sprains

Warnings

For external use only.

Avoid contact with eyes.

Flammable: keep away from fire or flame.

When using this product

- use only as directed
- do not bandage tightly or use with heating pad
- do not apply to wounds or damaged skin

Stop use and ask doctor if

- condition worsens, or if symptoms persist for more than 7 days or clear up and occur again within a few days
- redness is present
- excessive irritation of the skin develops

If pregnant or breastfeeding,

ask a health professional before use.

Keep out of reach of children.

If swallowed, get medical helop or contact a Poison Control Center right away.

Directions

Adults and children over 12 years:

apply directly onto affected area without the need to bandage
repeat if necessary, but do not apply more than 4 times daily.

Children 12 years or younger:

ask a doctor.

Other information

- store at room temperature

Inactive ingredients

acrylic acid/vinyl ester copolymer, dimethylsulfone (MSM), eucalyptus oil, glucosamine sulfate, hydroxypropylcellulose, SD alcohol 39C, PEG-8 dimethicone, pentylene glycol, peppermint oil, triethanolamine, water (USP).

Manufacturing Information

Manufactured for:

Medline Industries, LP

Three Lakes Drive, Northfield, IL 60093 USA

Made in USA

www.medline.com

1-800-MEDLINE (633-5463)

REF: MDSAICEGEL, MDSAICEGELR

V3 RF23MFO, V4 RC22MFO